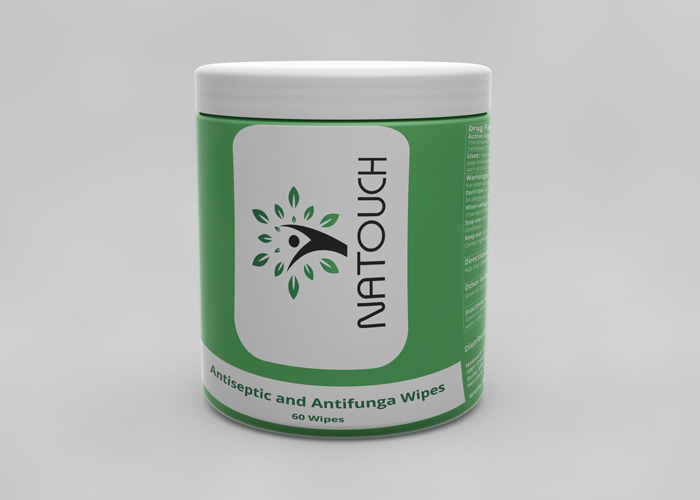 DRUG LABEL: Natouch Eczema Wipes
NDC: 79073-030 | Form: CLOTH
Manufacturer: Natouch LLC
Category: otc | Type: HUMAN OTC DRUG LABEL
Date: 20260210

ACTIVE INGREDIENTS: OATMEAL 3 g/200 mL
INACTIVE INGREDIENTS: SOPHORA FLAVESCENS WHOLE 0.292 g/200 mL; SCUTELLARIA BAICALENSIS ROOT 0.292 g/200 mL; PHELLODENDRON AMURENSE BARK 0.292 g/200 mL; ATRACTYLODES MACROCEPHALA WHOLE 0.292 g/200 mL; WATER 146 g/200 mL; ALOE VERA LEAF 2 g/200 mL; ROSA RUGOSA FLOWER 10 g/200 mL; DICTAMNUS DASYCARPUS ROOT BARK 0.292 g/200 mL; FU LING 0.292 g/200 mL; BORNEOL 0.097 g/200 mL; PELARGONIUM GRAVEOLENS FLOWERING TOP 0.292 g/200 mL; MELALEUCA ALTERNIFOLIA LEAF 0.292 g/200 mL; GLYCERIN 2 g/200 mL; CENTELLA ASIATICA 0.292 g/200 mL; COPTIS CHINENSIS WHOLE 0.049 g/200 mL; BASSIA SCOPARIA FRUIT 0.146 g/200 mL; CNIDIUM MONNIERI FRUIT 0.486 g/200 mL; TRIFOLIUM PRATENSE FLOWER 0.292 g/200 mL

Natouch Eczema Wipes

This is a hand sanitizer manufactured according to the Temporary Policy for Preparation of Certain Alcohol-Based Hand Sanitizer Products During the Public Health Emergency (CoViD-19); Guidance for Industry.

The hand sanitizer is manufactured using only the following United States Pharmacopoeia (USP) grade ingredients in the preparation of the product (percentage in final product formulation) consistent with World Health Organization (WHO) recommendations:

1. Alcohol (ethanol) (USP or Food Chemical Codex (FCC) grade) (80%, volume/volume (v/v)) in an aqueous solution denatured according to Alcohol and Tobacco Tax and Trade Bureau regulations in 27 CFR part 20.
2. Glycerol (1.45% v/v).
3. Hydrogen peroxide (0.125% v/v).
4. Sterile distilled water or boiled cold water.

The firm does not add other active or inactive ingredients. Different or additional ingredients may impact the quality and potency of the product.

Purpose

Antiseptic, Antifungal Wet Wipes

Use

Wet Wipes to help reduce microbes that potentially can cause disease. For use when soap and water are not available. Also can be used for treat skin disease caused by fungus, such as jock itch, athlete's foot or ringworm.

Warnings

For external use only. Flammable. Keep away from heat or flame

Do not use

- in children less than 2 months of age
- on open skin wounds
- You are known to be allergy to any ingredients.

When using this product keep out of eyes, ears, and mouth. In case of contact with eyes, rinse eyes thoroughly with water.
Stop use and ask a doctor if irritation or rash occurs. These may be signs of a serious condition.
Keep out of reach of children. If swallowed, get medical help or contact a Poison Control Center right away.

Stop use and ask a doctor if irritation or rash occurs. These may be signs of a serious condition.

Keep out of reach of children. If swallowed, get medical help or contact a Poison Control Center right away.

Directions

- Rub the sheet on certain skin areas needed to be cleaned or infected with fungus

Other Information

Store at 20-25oC (68-77 oF). Avoid Excessive Moisture.

Inactive ingredients

glycerin,Menthol, Eucalyptol, Propylene Glycol, Glycerol, lavender oil, Aloe Vera, purified water USP

Dosage and Administration

Rub the sheet on certain skin areas.
Supervise children under 6 years of age when using this product to avoid swallowing.

Package Label - Principal Display Panel

60 sheets Canister NDC: 79073-001-60